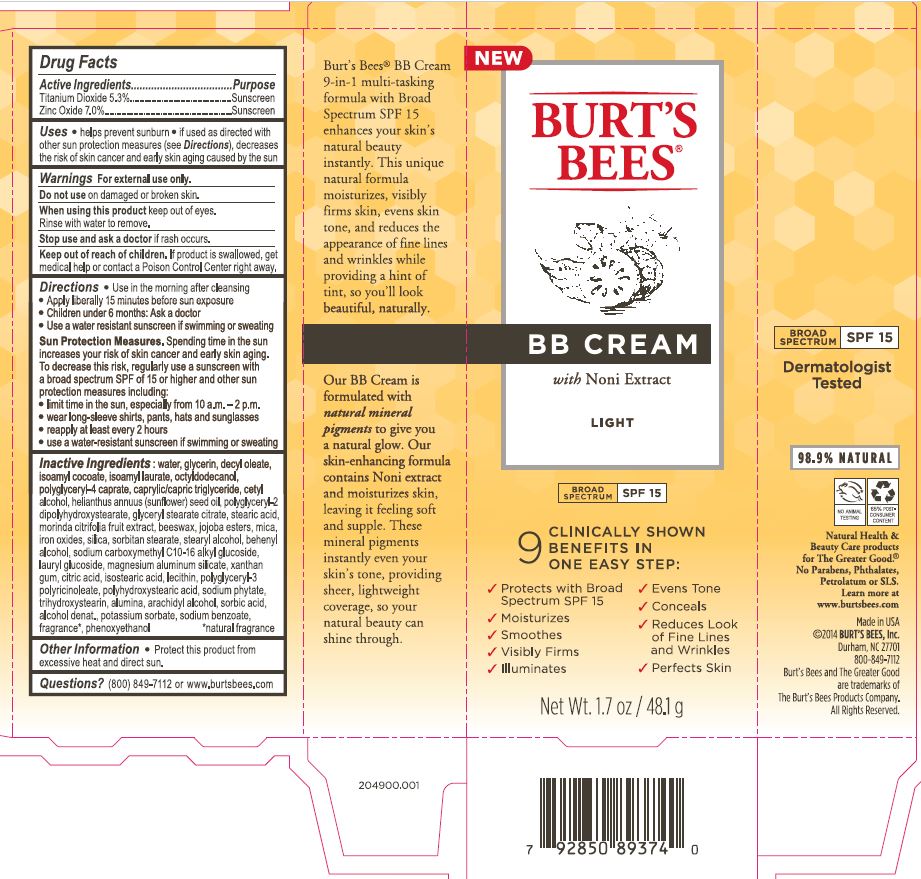 DRUG LABEL: BB Broad Spectrum SPF 15 Light
NDC: 26052-030 | Form: CREAM
Manufacturer: Burt's Bees
Category: otc | Type: HUMAN OTC DRUG LABEL
Date: 20231005

ACTIVE INGREDIENTS: TITANIUM DIOXIDE 5.3 g/100 g; ZINC OXIDE 7 g/100 g
INACTIVE INGREDIENTS: ISOAMYL LAURATE; WATER; GLYCERIN; MAGNESIUM ALUMINUM SILICATE; XANTHAN GUM; CETYL ALCOHOL; POLYGLYCERYL-2 DIPOLYHYDROXYSTEARATE; YELLOW WAX; STEARIC ACID; MORINDA CITRIFOLIA FRUIT; MICA; SILICON DIOXIDE; TRICAPRIN; SORBITAN MONOSTEARATE; STEARYL ALCOHOL; LAURYL GLUCOSIDE; ALCOHOL; POTASSIUM SORBATE; SODIUM BENZOATE; PHYTATE SODIUM; ISOAMYL COCOATE; FERRIC OXIDE RED; LECITHIN, SOYBEAN; POLYGLYCERYL-3 RICINOLEATE; TRIHYDROXYSTEARIN; ALUMINUM OXIDE; ARACHIDYL ALCOHOL; SORBIC ACID; CITRIC ACID MONOHYDRATE; DECYL OLEATE; PHENOXYETHANOL; POLYHYDROXYSTEARIC ACID (2300 MW); OCTYLDODECANOL; POLYGLYCERYL-4 CAPRATE; SUNFLOWER OIL; GLYCERYL STEARATE CITRATE; DOCOSANOL; JOJOBA OIL; ISOSTEARIC ACID

BB Cream Broad Spectrum SPF 15 Light

Active Ingredients

Titanium Dioxide 5.3%

Zinc Oxide 7.0%

PURPOSE

Sunscreen

Uses

- helps prevent sunburn
- if used as directed with other sun protection measures (see Directions), decreases the risk of skin cancer and early skin again caused by the sun

Warnings

For external use only.

Do not use on damaged or broken skin.

When using this product keep out of eyes.

Rinse with water to remove.

Stop use and ask a doctor if rash occurs.

Keep out of reach of children.

If product is swallowed, get medical help or contact a Poison Control Center right away.

Directions

- Use in the morning after cleansing
- Apply liberally 15 minutes before sun exposure
- Children under 6 months: Ask a doctor
- Use a water resisitant sunscreen if swimming or sweating

Sun Protection Measures. Spending time in the sun increases your risk of skin cancer and early skin aging. To decrease this risk, regularly use a sunscreen with a broad spectrum SPF of 15 or higher and other sun protection measures including:

- limit time in the sun, especially from 10 a.m. to 2 p.m.
- wear long sleeve shirts, pants, hats and sunglasses
- reapply at least every two hours
- use a water resistant sunscreen if swimming or sweating

INACTIVE INGREDIENT

Inactive Ingredients: water, glycerin, decyl oleate, isoamyl cocoate, isoamyl laurate, octyldodecanol, polyglyceryl-4 caprate, caprylic/capric triglyceride, cetyl alcohol, helianthus annuus (sunflower) seed oil, poylglyceryl-2 dipolyhydroxystearate, glyceryl stearate citrate, stearic acid, morinda citrifolia fruit extract, beeswax, jojoba esters, mica, iron oxides, silica, sorbitan stearate, stearyl alcohol, behenyl alcohol, sodium carboxymethyl C10-16 alkyl glucoside, lauryl glucoside, magnesium aluminum silicate, xanthan gum, citric acid, isostearic acid, lecithin, polyglyceryl-3 polyricinoleate, polyhydroxystearic acid, sodium phytate, trihydroxysearin, alumina, arachidyl alcohol, sorbic acid, alcohol denat., potassium sorbate, sodium benzoate, fragrance*, phenoxylethanol

*natural fragrance

Other Information

- Protect this product from excessive heat and direct sun

Questions?

- (800) 849-7112 or www.burtsbees.com

PACKAGE LABEL

Burt's Bees

BB CREAM

with Noni Extract

LIGHT

Broad Spectrum SPF 15

Net Wt. 1.7 oz / 48.1 g